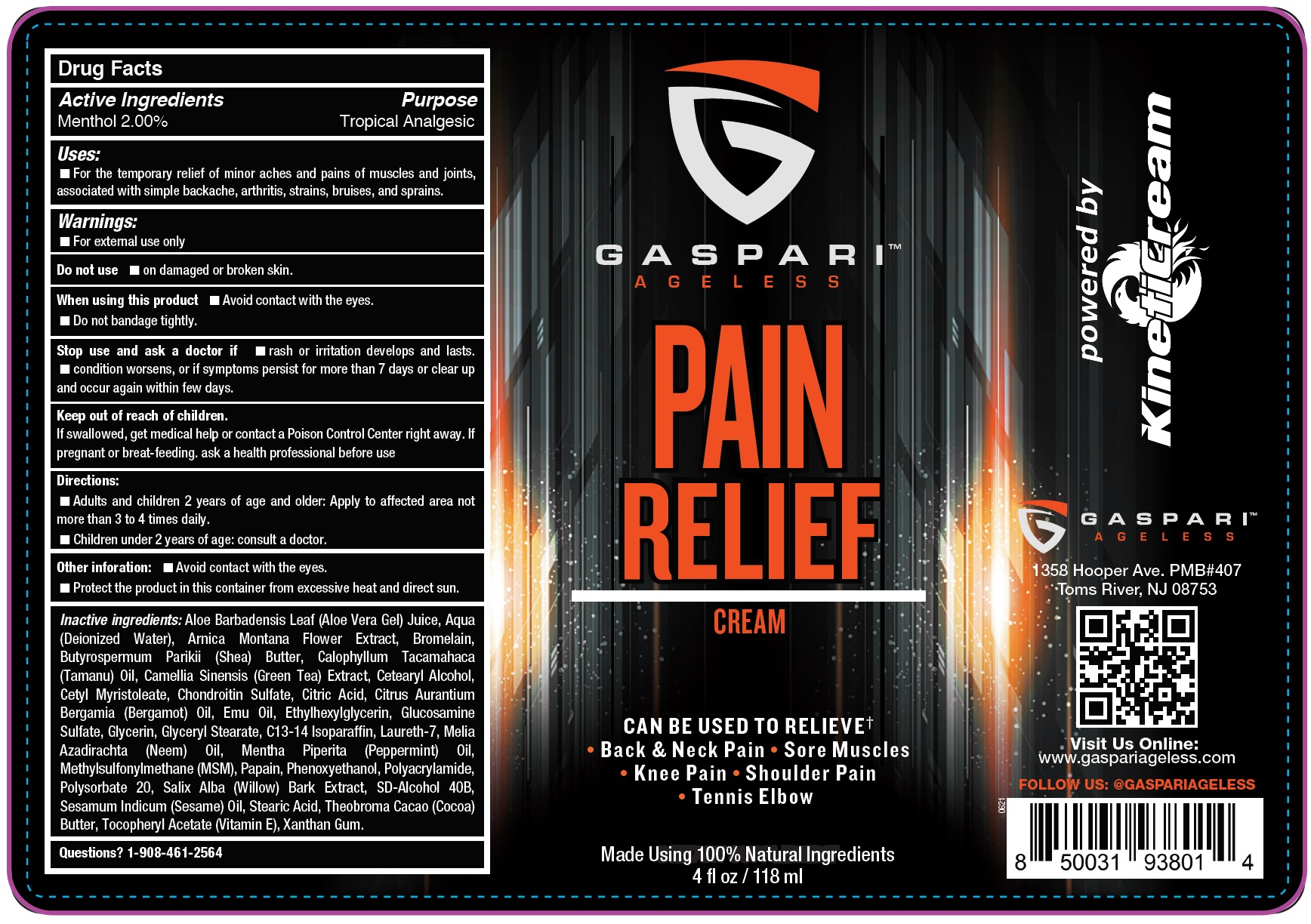 DRUG LABEL: GASPARI Ageless Pain Relief Cream
NDC: 82262-224 | Form: CREAM
Manufacturer: GASPARI ANTI-AGING LLC
Category: otc | Type: HUMAN OTC DRUG LABEL
Date: 20231111

ACTIVE INGREDIENTS: MENTHOL 20 mg/1 mL
INACTIVE INGREDIENTS: ALOE VERA LEAF; WATER; ARNICA MONTANA FLOWER; BROMELAINS; SHEA BUTTER; TAMANU OIL; GREEN TEA LEAF; CETOSTEARYL ALCOHOL; CETYL MYRISTOLEATE; CITRIC ACID MONOHYDRATE; BERGAMOT OIL; EMU OIL; ETHYLHEXYLGLYCERIN; GLUCOSAMINE SULFATE; GLYCERIN; GLYCERYL MONOSTEARATE; C13-14 ISOPARAFFIN; LAURETH-7; PEPPERMINT OIL; DIMETHYL SULFONE; PAPAIN; PHENOXYETHANOL; POLYSORBATE 20; SALIX ALBA BARK; SESAME OIL UNSAPONIFIABLES; STEARIC ACID; COCOA; .ALPHA.-TOCOPHEROL ACETATE; XANTHAN GUM

GASPARI Ageless Pain Relief Cream

Active Ingredients

Menthol 2.00%

Purpose

Tropical Analgesic

Uses:

- For the temporary relief of minor aches and pains of muscles and joints, associated with simple backache, arthritis, strains, bruises, and sprains.

Warnings:

- For external use only

Do not use

- on damaged or broken skin.

When using this product

- Avoid contact with the eyes.
- Do not bandage tightly.

Stop use and ask a doctor if

rash or irritation develops and lasts. condition worsens, or if symptoms persist for more than 7 days or clear up and occur again within few days.

Keep out of reach of children.

If swallowed, get medical help or contact a Poison Control Center right away. If pregnant or breat-feeding. ask a health professional before use

Directions:

- Adults and children 2 years of age and older: Apply to affected area not ore than 3 to 4 times daily.
- Children under 2 years of age: consult a doctor.

Other inforation:

- Avoid contact with the eyes.
- Protect the product in this container from excessive heat and direct sun.

Inactive ingredients:

Aloe Barbadensis Leaf (Aloe Vera Gel) Juice, Aqua (Deionized Water), Arnica Montana Flower Extract, Bromelain, Butyrospermum Parikii (Shea) Butter, Calophyllum Tacamahaca (Tamanu) Oil, Camellia Sinensis (Green Tea) Extract, Cetearyl Alcohol, Cetyl Myristoleate, Chondroitin Sulfate, Citric Acid, Citrus Aurantium Bergamia (Bergamot) Oil, Emu Oil, Ethylhexylglycerin, Glucosamine Sulfate, Glycerin, Glyceryl Stearate, C13-14 Isoparaffin, Laureth-7, Melia Azadirachta (Neem) Oil, Mentha Piperita (Peppermint) Oil, Methylsulfonylmethane (MSM), Papain, Phenoxyethanol, Polyacrylamide, Polysorbate 20, Salix Alba (Willow) Bark Extract, SD-Alcohol 40B, Sesamum Indicum (Sesame) Oil, Stearic Acid, Theobroma Cacao (Cocoa) Butter, Tocopheryl Acetate (Vitamin E), Xanthan Gum.

Questions?

1-908-461-2564